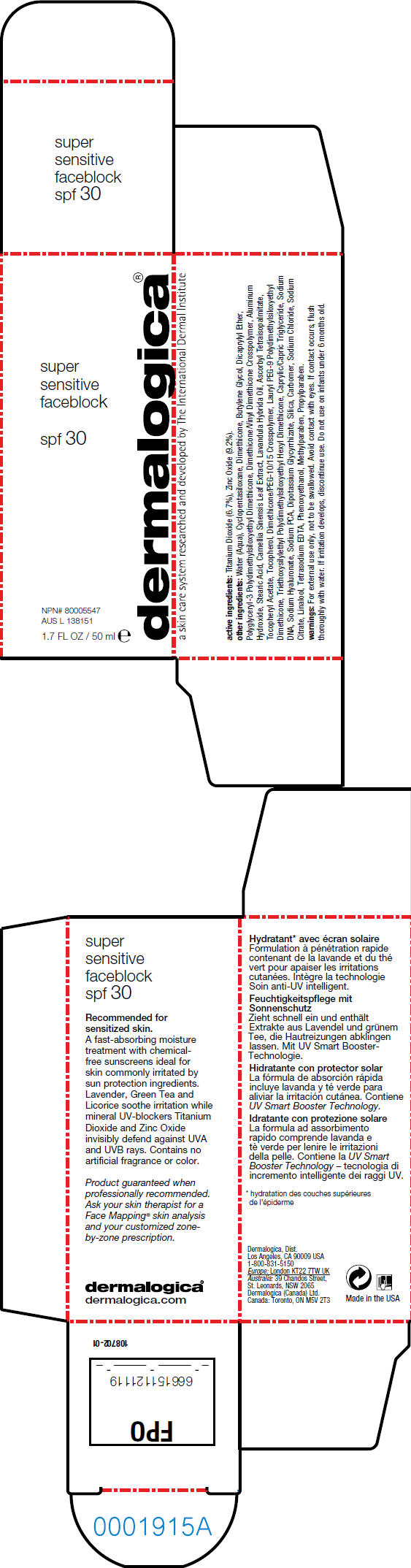 DRUG LABEL: FACEBLOCK 
NDC: 21839-111 | Form: LOTION
Manufacturer: Gordon Laboratories, Inc
Category: otc | Type: HUMAN OTC DRUG LABEL
Date: 20110318

ACTIVE INGREDIENTS: Titanium Dioxide 3.35 mL/50 mL; Zinc Oxide 4.6 mL/50 mL
INACTIVE INGREDIENTS: Water; Cyclomethicone 5; Dimethicone; Butylene Glycol; Dicaprylyl Ether; Aluminum Hydroxide; Stearic Acid; Green Tea Leaf; Lavandin Oil; Alpha-Tocopherol; Medium-Chain Triglycerides; Hyaluronate Sodium; Sodium Pyrrolidone Carboxylate; Silicon Dioxide; Sodium Chloride; Sodium Citrate; Linalool, Dl-; Edetate Sodium; Phenoxyethanol; Methylparaben; Propylparaben

dermalogica®
super
sensitive
faceblock

active ingredients

Titanium Dioxide (6.7%), Zinc Oxide (9.2%).

other ingredients

Water (Aqua), Cyclopentasiloxane, Dimethicone, Butylene Glycol, Dicaprylyl Ether, Polyglyceryl-3 Polydimethylsiloxyethyl Dimethicone, Dimethicone/Vinyl Dimethicone Crosspolymer, Aluminum Hydroxide, Stearic Acid, Camellia Sinensis Leaf Extract, Lavandula Hybrida Oil, Ascorbyl Tetraisopalmitate, Tocopheryl Acetate, Tocopherol, Dimethicone/PEG-10/15 Crosspolymer, Lauryl PEG-9 Polydimethylsiloxyethyl Dimethicone, Triethoxysilylethyl Polydimethylsiloxyethyl Hexyl Dimethicone, Caprylic/Capric Triglyceride, Sodium DNA, Sodium Hyaluronate, Sodium PCA, Dipotassium Glycyrrhizate, Silica, Carbomer, Sodium Chloride, Sodium Citrate, Linalool, Tetrasodium EDTA, Phenoxyethanol, Methylparaben, Propylparaben.

warnings

For external use only, not to be swallowed.

WHEN USING

Avoid contact with eyes. If contact occurs, flush thoroughly with water.

If irritation develops, discontinue use.

Do not use on infants under 6 months old.

PRINCIPAL DISPLAY PANEL - 50 ml Carton

super
sensitive
faceblock

spf 30

NPN# 80005547
AUS L 138151

1.7 FL OZ / 50 ml e

dermalogica®